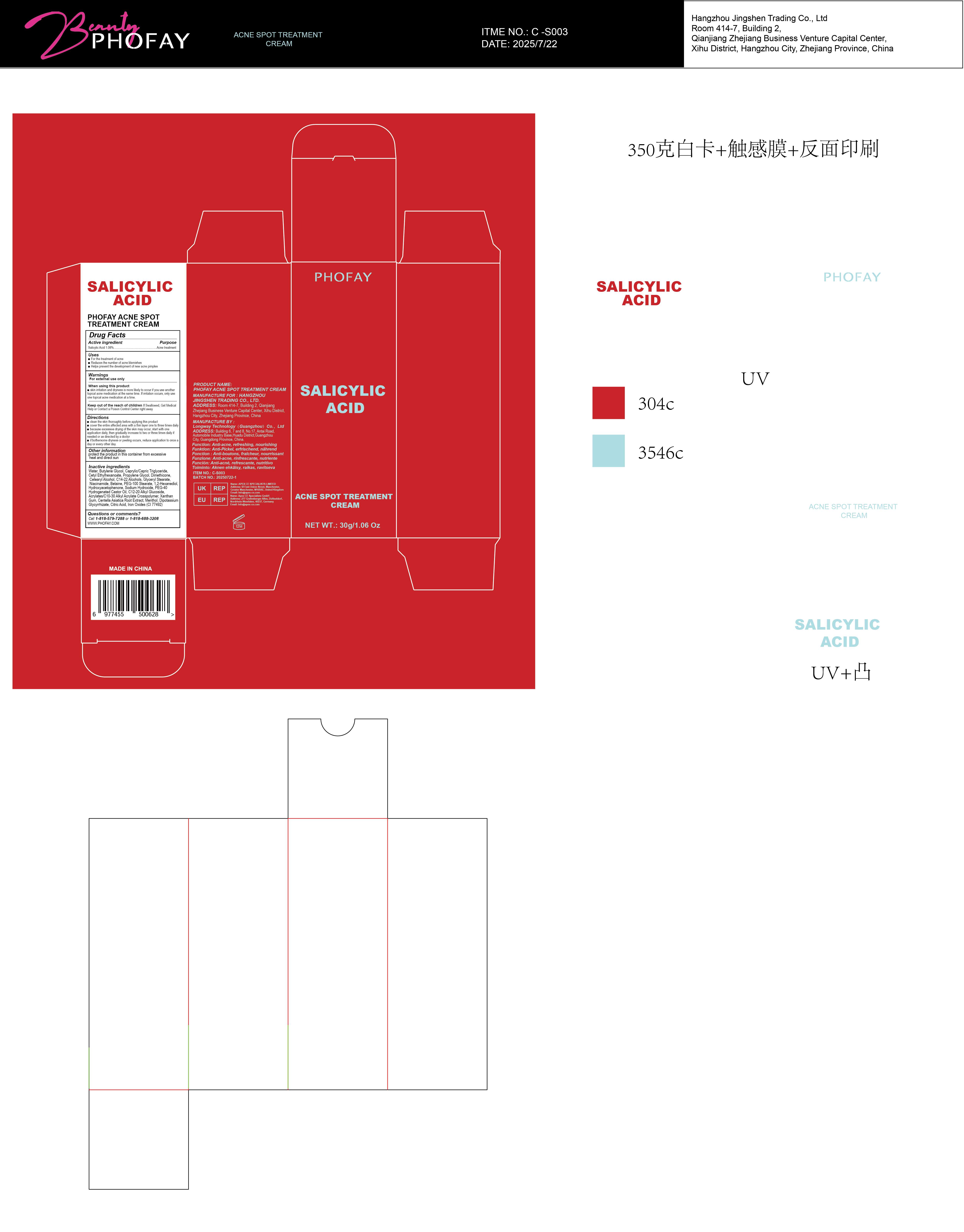 DRUG LABEL: PHOFAY ACNE SPOTTREATMENT Cream
NDC: 87080-101 | Form: CREAM
Manufacturer: Hangzhou Jingshen Trading Co., Ltd.
Category: otc | Type: HUMAN OTC DRUG LABEL
Date: 20250826

ACTIVE INGREDIENTS: SALICYLIC ACID 0.0108 g/1 g
INACTIVE INGREDIENTS: HYDROXYACETOPHENONE; DIPOTASSIUM GLYCYRRHIZATE; DIPROPYLENE GLYCOL; CETEARYL ALCOHOL; C14-22 ALCOHOLS; PEG-40 HYDROGENATED CASTOR OIL; DIMETHICONE; CENTELLA ASIATICA ROOT; SODIUM HYDROXIDE; NIACINAMIDE; C12-20 ALKYL GLUCOSIDE; MENTHOL; CETYL ETHYLHEXANOATE; WATER; BUTYLENE GLYCOL; PEG-100 STEARATE; 1,2-HEXANEDIOL; ACRYLATES/C10-30 ALKYL ACRYLATE CROSSPOLYMER (60000 MPA.S); XANTHAN GUM; CAPRYLIC/CAPRIC TRIGLYCERIDE; BETAINE; CITRIC ACID; CI 77492; GLYCERYL STEARATE

ACTIVE INGREDIENT

SALICYLIC ACID1.08%

KEEP OUT OF REACH OF CHILDREN

lf Swallowed, Get Medica Help or Contact a Poison Control Center right away

WARNINGS

For external use only
When using this product

skin irritation and dryness is more likely to occur if you use another topical acne medication at the same time. lf irritation occurs, only use one topical acne medication at a time.

Directions
clean the skin thoroughly before applying this product

cover the entire affected area with a thin layer one to three times daily

because excessive drying of the skin may occur, start with one application daily, then gradually increase to two or three times daily if needed or as directed by a doctor

if bothersome dryness or peeling occurs, reduce application to once a day or every other day.

INACTIVE INGREDIENT

Water, Butylene Glycol, Caprylic/Capric Triglyceride,Cetyl Ethylhexanoate, Propylene Glycol, Dimethicone Cetearyl Alcohol, C14-22 Alcohols, Glyceryl Stearate，Niacinamide, Betaine,PEG-100 Stearate, 1,2-Hexanediol,Hydroxyacetophenone, Sodium Hydroxide, PEG-40 Hydrogenated Castor Oil, C12-20 Alkyl Glucoside,Acrylates/C10-30 Alkyl Acrylate Crosspolymer, Xanthan Gum,Centella Asiatica Root Extract, Menthol, Dipotassium Glycyrrhizate, Citric Acid, lron Oxides (Cl 77492)

OTHER SAFETY INFORMATION

protect the product in this container from excessive

heat and direct sun

PURPOSE

Acne treatment

INDICATIONS AND USAGE

For the treatment of acne
Reduces the number of acne blemishes

Helps prevent the development of new acne pimples

QUESTIONS

Call 1-818-579-7288 or 1-818-688-3208

WWW.PHOFAY.COM